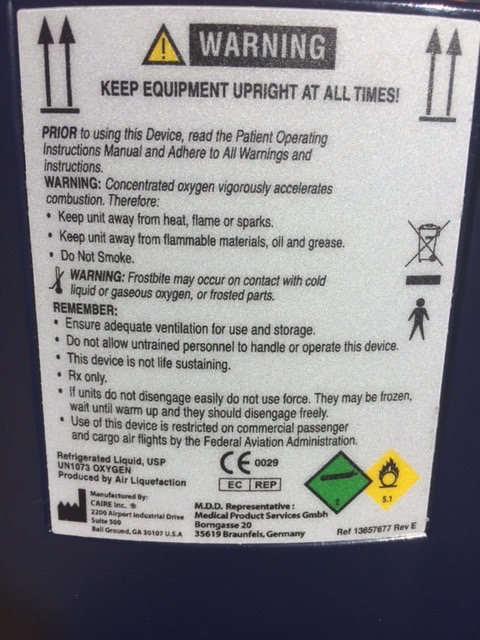 DRUG LABEL: Oxygen
NDC: 70376-001 | Form: GAS
Manufacturer: Metro Aire LTD
Category: prescription | Type: HUMAN PRESCRIPTION DRUG LABEL
Date: 20171210

ACTIVE INGREDIENTS: OXYGEN 990 L/1 L

Oxygen

PACKAGE LABEL

WARNING KEEP EQUIPMENT UPRIGHT AT ALL TIMES!

PRIOR to using this Device, read the Patient Operating Instruction Manual and Adhere to All Warnings and instructions.

WARNING: Concentrated oxygen vigorously accelerates combustion. Therefore: . Keep unit away from heat, flame or sparks. . Keep unit away from flammable materials, oil and grease. . Do Not Smoke.

WARNING: Frosbite may occur on contact with cold liquid or faseous oxygen, or frosted parts.

REMEMBER: . Ensure adequate ventilation for use and storage. . Do not allow untrained personnel to handle or operate this device. . This device is not life sustaining. . Rx only. . If units do not desengage easily do not use force. They may be frozen, wait until warm up and they should disengage freely. . Use of this device is restricted on commercial passenger and cargo air flights by the Federal Aviation Administration.

Refrigerated Liquid, USP UN1073 OXYGEN Produced by Air Liquefaction C E 0029 EC REP non-flammable cylinder symbol 2 oxidizer symbol 5.1

Manufactured by: CAIRE Inc. 2200 Airport Industrial Drive Suite 300 Ball Ground, GA 30107 U.S.A. M.D.D. Representative: Medical Product Services Gmbh Borngasse 20 35619 Braunfels, Germany Ref 13657677 Rev E